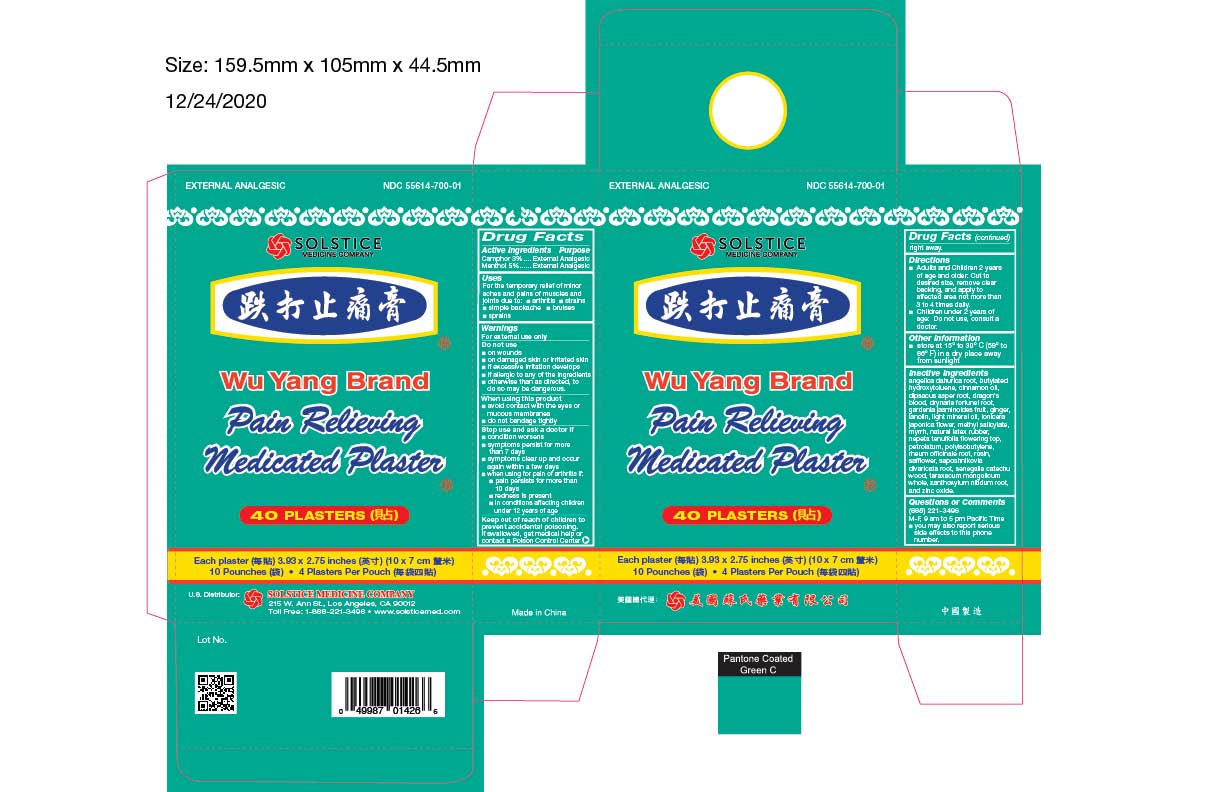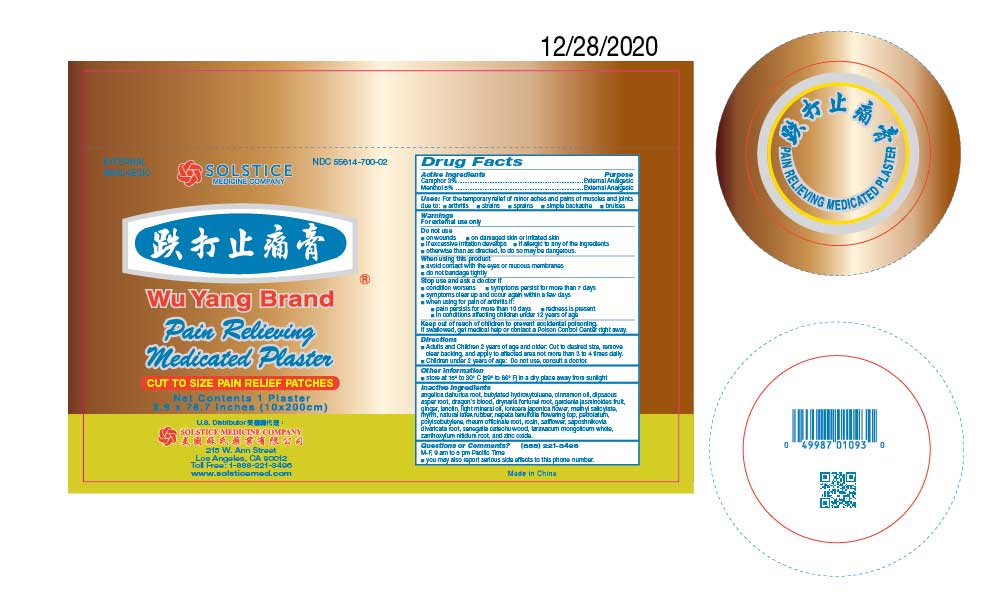 DRUG LABEL: WU YANG BRAND PAIN RELIEVING MEDICATED
NDC: 55614-700 | Form: PLASTER
Manufacturer: MADISON ONE ACME INC
Category: otc | Type: HUMAN OTC DRUG LABEL
Date: 20251110

ACTIVE INGREDIENTS: MENTHOL 5 g/100 g; CAMPHOR (SYNTHETIC) 3 g/100 g
INACTIVE INGREDIENTS: ANGELICA DAHURICA ROOT; BUTYLATED HYDROXYTOLUENE; CINNAMON OIL; DIPSACUS ASPER ROOT; DRAGON'S BLOOD; DRYNARIA FORTUNEI ROOT; GARDENIA JASMINOIDES FRUIT; GINGER; LANOLIN; LIGHT MINERAL OIL; LONICERA JAPONICA FLOWER; METHYL SALICYLATE; MYRRH; NATURAL LATEX RUBBER; NEPETA TENUIFOLIA FLOWERING TOP; PETROLATUM; POLYISOBUTYLENE (800000 MW); RHEUM OFFICINALE ROOT; ROSIN; SAFFLOWER; SAPOSHNIKOVIA DIVARICATA ROOT; SENEGALIA CATECHU WOOD; TARAXACUM MONGOLICUM WHOLE; ZANTHOXYLUM NITIDUM ROOT; ZINC OXIDE

Drug Facts

Active ingredients
Menthol 5%
Camphor 3%

Purpose
External analgesic
External analgesic

Uses
For the temporary relief of minor aches and pains of muscles and joints due to:
■ arthritis
■ strains
■ simple backache
■ bruises
■ sprains

Warnings
For external use only

Do not use
■ on wounds
■ on damaged or irritated skin
■ if excessive irritation develops
■ otherwise than as directed, to do so may be dangerous

When using this product
■ avoid contact with the eyes or mucous membranes
■ do not bandage tightly

Stop use and ask a doctor if
■ condition worsens
■ symptoms persist for more than 7 days
■ symptoms clear up and occur again within a few days
■ when using for pain of arthritis if:
■ pain persists for more than 10 days
■ redness is present
■ in conditions affecting children under 12 years of age

KEEP OUT OF REACH OF CHILDREN

Keep out of reach of childrento avoid accidental poisoning. If swallowed, get medical help or contact a Poison Control Center right away.

Directions
■ Adults and children 2 years of age and older: Cut to desired size, remove clear backing, and apply to affected area not more than 3 to 4 times daily.
■ Children under 2 years of age: Do not use, consult a doctor.

Other information
■ store at 15º to 30º C (59º to 86º F) in a dry place away from sunlight

Inactive ingredients
angelica dahurica root, butylated hydroxytoluene, cinnamon oil, dipsacus asper root, dragon's blood, drynaria fortunei root, gardenia jasminoides fruit, ginger, lanolin, light mineral oil, lonicera japonica flower, methyl salicylate, myrrh, natural latex rubber, nepeta tenuifolia flowering top, petrolatum, polyisobutylene, rheum officinale root, rosin, safflower, saposhnikovia divaricata root, senegalia catechu wood, taraxacum mongolicum whole, zanthoxylum nitidum root and zinc oxide.

Questions or comments?(888) 221-3496 M-F 9 am to 5 pm
■ you may also report serious side effects to this phone number

PACKAGE LABEL

WU YANG BRAND PAIN RELIEVING MEDICATED PLASTER

External Analgesic

NDC 55614-700-01

Large Pain Relief Patches

10 Plasters
Each plaster 3.9 x 11 inches (10 x 28 cm) - 1 Plaster per pouch

PACKAGE LABEL

WU YANG BRAND PAIN RELIEVING MEDICATED PLASTER

External Analgesic

NDC 55614-700-02

Cut To Size Pain Relief Patches

1 Plaster
3.9 x 78.7 inches (10 x 200 cm)